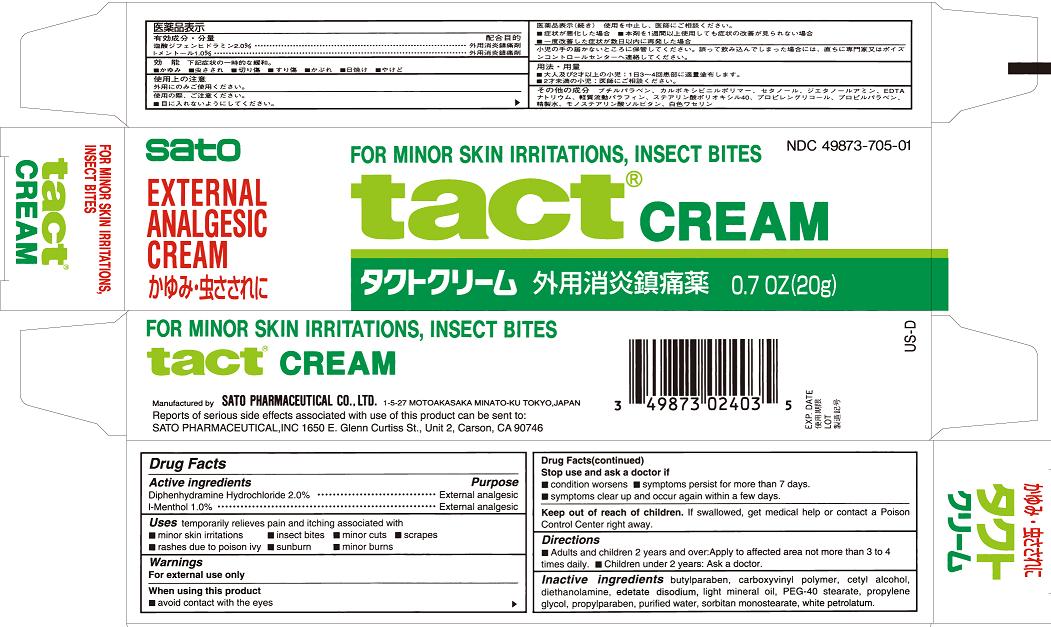 DRUG LABEL: TACT
NDC: 49873-705 | Form: CREAM
Manufacturer: Sato Pharmaceutical Inc., Ltd.
Category: otc | Type: HUMAN OTC DRUG LABEL
Date: 20231204

ACTIVE INGREDIENTS: DIPHENHYDRAMINE HYDROCHLORIDE 2 g/100 g; LEVOMENTHOL 1 g/100 g
INACTIVE INGREDIENTS: DIETHANOLAMINE; EDETATE SODIUM; LIGHT MINERAL OIL; PEG-40 STEARATE; PROPYLENE GLYCOL; PROPYLPARABEN; WATER; SORBITAN MONOSTEARATE; PETROLATUM; BUTYLPARABEN; CARBOMER HOMOPOLYMER TYPE C; CETYL ALCOHOL

Tact Cream

Active ingredients
Diphenhydramine hydrochloride 2.0%
Menthol 1.0%

Purpose
Diphenhydramine Hydrochloride External analgesic
l-Menthol External analgesic

Uses
temporarily relieves pain and itching associated with
■ minor skin irritations ■ insect bites ■ minor cuts ■ scrapes
■ rashes due to poison ivy ■ sunburn ■ minor burns

Warnings
For rectal use only

When using this product
■ avoid contact with the eyes

Stop use and ask a doctor if
■ condition worsens ■ symptoms persist for more than 7 days.
■ symptoms clear up and occur again within a few days.

Keep out of reach of children. If swallowed, get medical help or contact a Poison Control Center right away.

Directions
■ adults and children 2 years and over: Apply to affected area not more than 3 to 4 times daily.
■ children under 2 years: Ask a doctor.

INACTIVE INGREDIENT

Inactive ingredients butylparaben, carboxyvinyl polymer, cetyl alcohol, diethanolamine, edetate disodium, light mineral oil, PEG-40 stearate, propylene glycol, propylparaben, purified water, sorbitan monostearate, white petrolatum.

PACKAGE LABEL

tactcreamcart.jpg